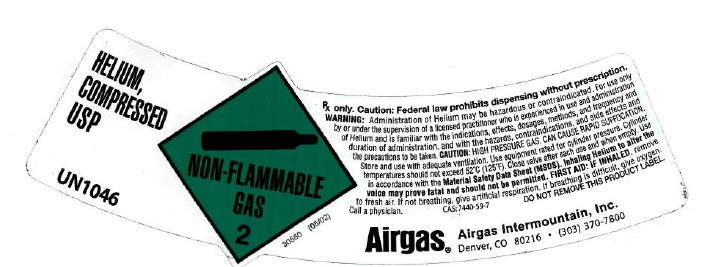 DRUG LABEL: Helium
NDC: 58420-004 | Form: GAS
Manufacturer: Airgas Intermountain Inc
Category: prescription | Type: HUMAN PRESCRIPTION DRUG LABEL
Date: 20100622

ACTIVE INGREDIENTS: Helium 992 mL/1 L

helium

PACKAGE LABEL

HELIUM, COMPRESSED USP
UN1046
NON-FLAMMABLE 2
30580 (05/02)
Rx only. CAUTION: Federal law prohibits dispensing without a prescription. WARNING: Administration of Helium may be hazardous or contraindicated. For use only by or under the supervision of a licensed practitioner who is experienced in the use and administration of Helium, and is familiar with the indications, effects, dosages, methods, and frequency and duration of administration, and with the hazards, contraindications and side effects, and the precautions to be taken.
CAUTION: HIGH PRESSURE GAS. CAN CAUSE RAPID SUFFOCATION. Store and use with adequate ventilation. Use equipment rated for cylinder pressure. Cylinder temperature should not exceed 52oC(125oF). Close valve after each use and when empty. Use in accordance with the Material Safety Data Sheet (MSDS). Inhaling Helium to alter the voice may prove fatal and should not be permitted. FIRST AID: IF INHALED, remove to fresh air. If not breathing, give artificial respiration. If breathing is difficult, give oxygen. Call a physician. C.A.S. : 7440-59-7 DO NOT REMOVE THIS PRODUCT LABEL.
AIRGAS PURITAN MEDICAL Distributed By: Airgas Intermountain, Inc. Denver, CO 80216 (303) 370-7800